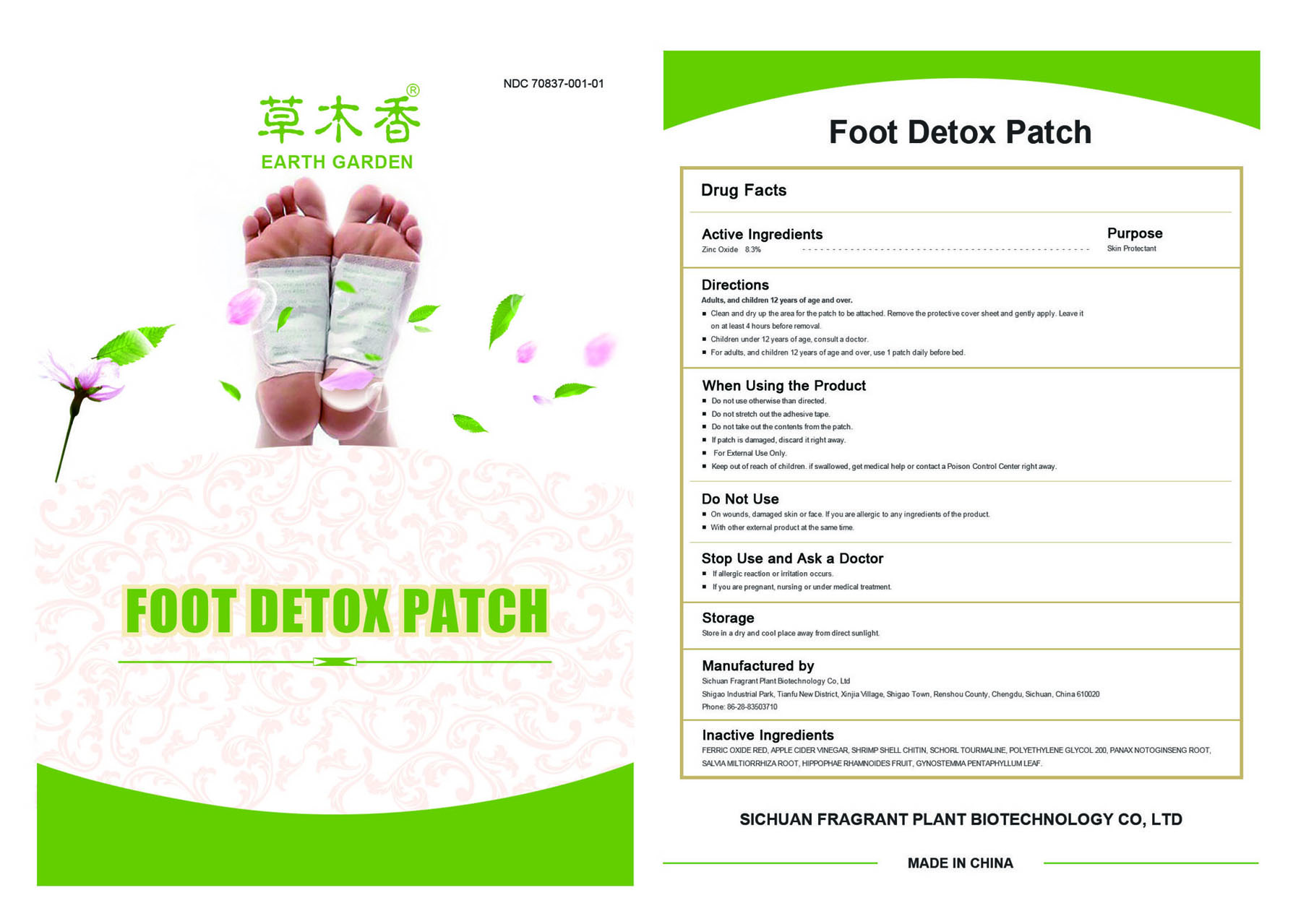 DRUG LABEL: FOOT DETOX
NDC: 70837-001 | Form: PATCH
Manufacturer: Sichuan Fragrant Plant Biotechnology Co, Ltd
Category: otc | Type: HUMAN OTC DRUG LABEL
Date: 20200117

ACTIVE INGREDIENTS: ZINC OXIDE 8.3 g/100 g
INACTIVE INGREDIENTS: FERRIC OXIDE RED; APPLE CIDER VINEGAR; SHRIMP SHELL CHITIN; SCHORL TOURMALINE; POLYETHYLENE GLYCOL 200; PANAX NOTOGINSENG ROOT; SALVIA MILTIORRHIZA ROOT; HIPPOPHAE RHAMNOIDES FRUIT; GYNOSTEMMA PENTAPHYLLUM LEAF

Sichuan Fragrant Plant Biotechnology Co, Ltd

Active Ingredients

Zinc Oxide 8.3%

Purpose

Zinc Oxide Skin Protectant

Directions

Adults, and children 12 years of age and over, clean and dry up the area for the patch to be attached. Remove the protective cover sheet and gently apply. Leave it on at least 4 hours before removal. Children under 12 years of age, consult a doctor.

DOSAGE AND ADMINISTRATION

For adults, and children 12 years of age and over, use 1 patch daily before bed.

When Using the Product

Do not use otherwise than directed.
Do not stretch out the adhesive tape.
Do not take out the contents from the patch.
If patch is damaged, discard it right away.

Warning

For External Use Only.

Keep out of reach of children. if swallowed, get medical help or contact a Poison Control Center right away.

Do Not Use

On wounds, damaged skin or face.
If you are allergic to any ingredients of the product.
With other external product at the same time.

Stop Use and Ask a Doctor

If allergic reaction or irritation occurs.
If you are pregnant, nursing or under medical treatment.

Storage

Store in a dry and cool place away from direct sunlight.

Manufactured by

Sichuan Fragrant Plant Biotechnology Co, Ltd

Shigao Industrial Park, Tianfu New District, Xinjia Village, Shigao Town, Renshou County, Chengdu, Sichuan, China 610020

Phone: 86-28-83503710

Inactive Ingredients

FERRIC OXIDE RED, APPLE CIDER VINEGAR, SHRIMP SHELL CHITIN, SCHORL TOURMALINE, POLYETHYLENE GLYCOL 200, PANAX NOTOGINSENG ROOT, SALVIA MILTIORRHIZA ROOT, HIPPOPHAE RHAMNOIDES FRUIT, GYNOSTEMMA PENTAPHYLLUM LEAF